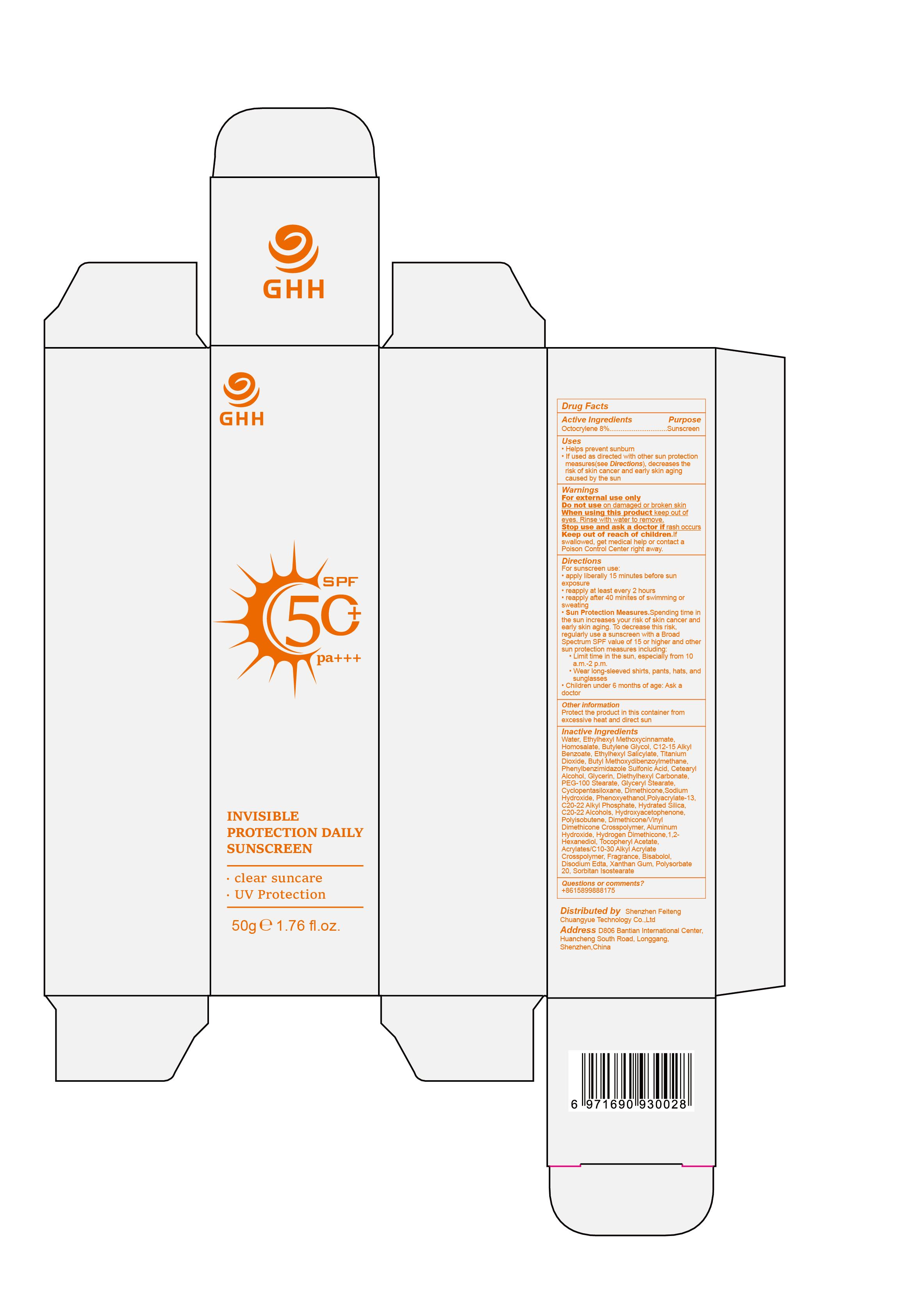 DRUG LABEL: GHH INVISIBLE PROTECTION DAILY SUNSCREEN
NDC: 75779-007 | Form: CREAM
Manufacturer: GUANG DONG 3 INS TECHNOLOGY Co., Ltd
Category: otc | Type: HUMAN OTC DRUG LABEL
Date: 20240618

ACTIVE INGREDIENTS: OCTOCRYLENE 8 g/100 g
INACTIVE INGREDIENTS: ACRYLATES/C10-30 ALKYL ACRYLATE CROSSPOLYMER (60000 MPA.S); WATER; HOMOSALATE; C20-22 ALKYL PHOSPHATE; DIMETHICONE/VINYL DIMETHICONE CROSSPOLYMER (SOFT PARTICLE); DIETHYLHEXYL CARBONATE; CETOSTEARYL ALCOHOL; OCTINOXATE; AVOBENZONE; ENSULIZOLE; HYDROGEN DIMETHICONE (13 CST); SORBITAN ISOSTEARATE; C20-22 ALCOHOLS; POLYISOBUTYLENE (1000 MW); EDETATE DISODIUM; POLYSORBATE 20; ALKYL (C12-15) BENZOATE; SODIUM HYDROXIDE; HYDRATED SILICA; HYDROXYACETOPHENONE; CYCLOMETHICONE 5; PHENOXYETHANOL; FRAGRANCE 13576; LEVOMENOL; XANTHAN GUM; BUTYLENE GLYCOL; OCTISALATE; POLYACRYLATE-13; ALUMINUM HYDROXIDE; 1,2-HEXANEDIOL; .ALPHA.-TOCOPHEROL ACETATE; GLYCERIN; POLYOXYL 100 STEARATE; GLYCERYL MONOSTEARATE; DIMETHICONE; TITANIUM DIOXIDE

75779-007

Active Ingredient

Octocrylene 8%

Purpose

Sunscreen

Use

Helps prevent sunburn
If used as directed with other sun protection measures(see Directions),decreases the risk of skin cancer and early skin aging caused by the sun

Warnings

For external use only

Do not use on damaged or broken skin

When Using

When using this product keep out of eyes. Rinse with water to remove.

Stop Use

Stop use and ask a doctor if rash occurs

Ask Doctor

Children under 6 months of age: Ask a doctor

Keep Oot Of Reach Of Children

Keep out of reach of children.If swallowed,get medical help or contact a Poison Control Center right away.

Directions

For sunscreen use:
apply liberally 15 minutes before sun exposure
reapply at least every 2 hours
reapply after 40 minites of swimming or sweating
Sun Protection Measures.Spending time in the sun increases your risk of skin cancer and early skin aging. To decrease this risk, regularly use a sunscreen with a Broad Spectrum SPF value of 15 or higher and other sun protection measures including:
Limit time in the sun, especially from 10 a.m.-2 p.m.
Wear long-sleeved shirts, pants, hats, and sunglasses
Children under 6 months of age: Ask a doctor

Other information

Protect the product in this container from excessive heat and direct sun

Inactive ingredients

Water,Ethylhexyl Methoxycinnamate,Homosalate,Butylene Glycol,C12-15 Alkyl Benzoate,Ethylhexyl Salicylate,Titanium Dioxide,Butyl Methoxydibenzoylmethane,Phenylbenzimidazole Sulfonic Acid,Cetearyl Alcohol,Glycerin,Diethylhexyl Carbonate,PEG-100 Stearate,Glyceryl Stearate,Cyclopentasiloxane,Dimethicone,Sodium Hydroxide,Phenoxyethanol,Polyacrylate-13,C20-22 Alkyl Phosphate,Hydrated Silica,C20-22 Alcohols,Hydroxyacetophenone,Polyisobutene,Dimethicone/Vinyl Dimethicone Crosspolymer,Aluminum Hydroxide,Hydrogen Dimethicone,1,2-Hexanediol,Tocopheryl Acetate,Acrylates/C10-30 Alkyl Acrylate Crosspolymer,Fragrance,Bisabolol,Disodium Edta,Xanthan Gum,Polysorbate 20,Sorbitan Isostearate

Questions

+8615899888175